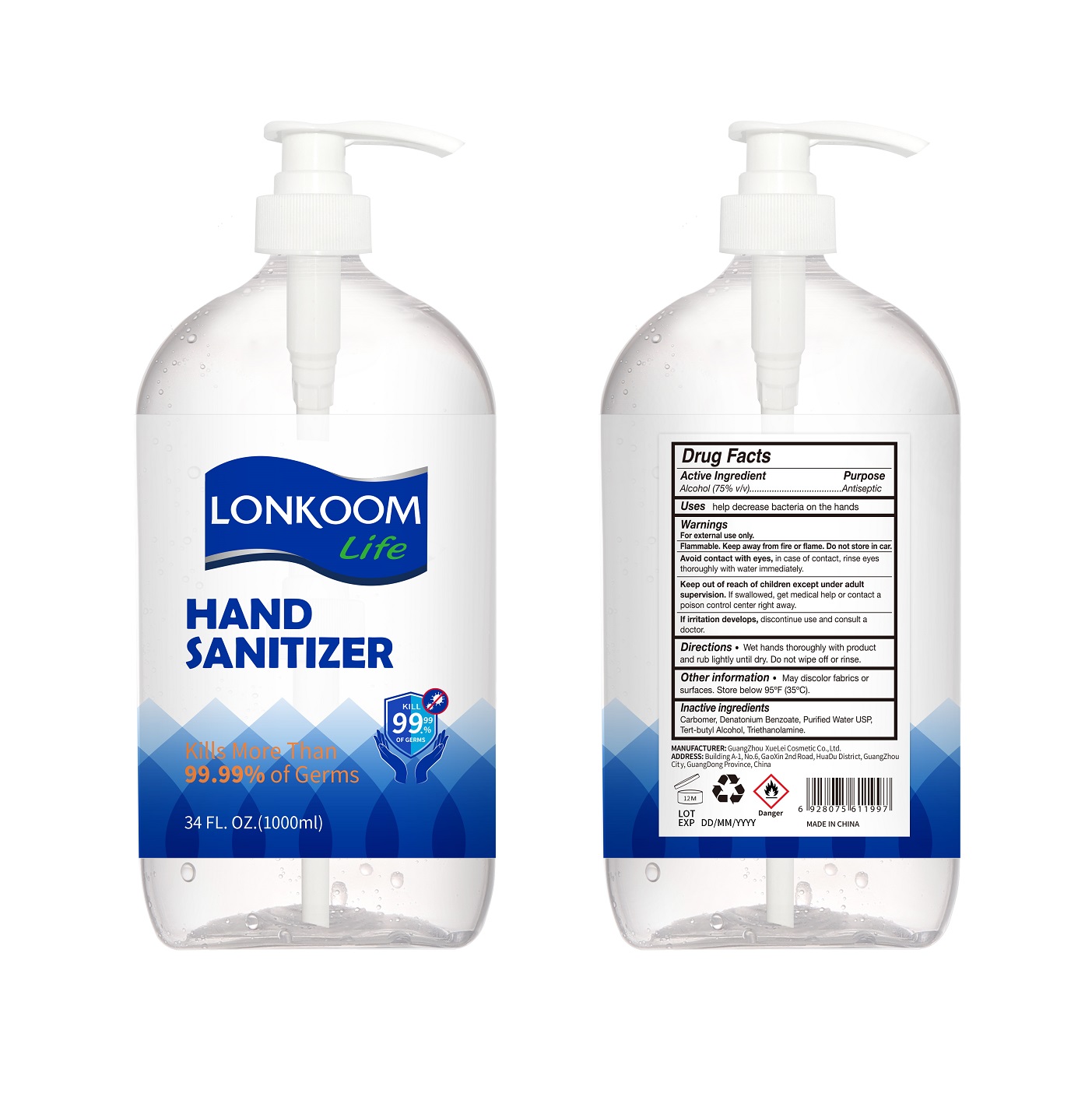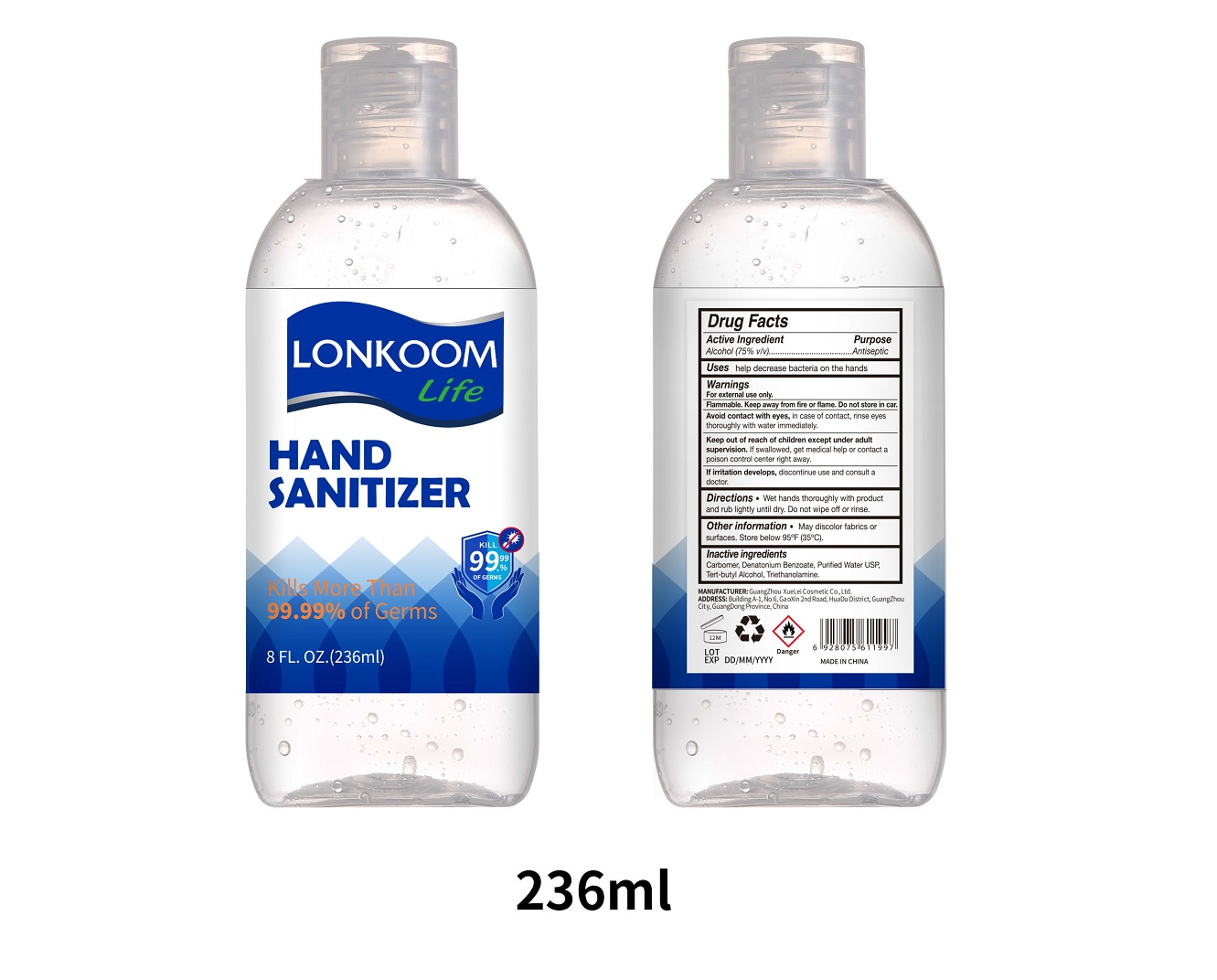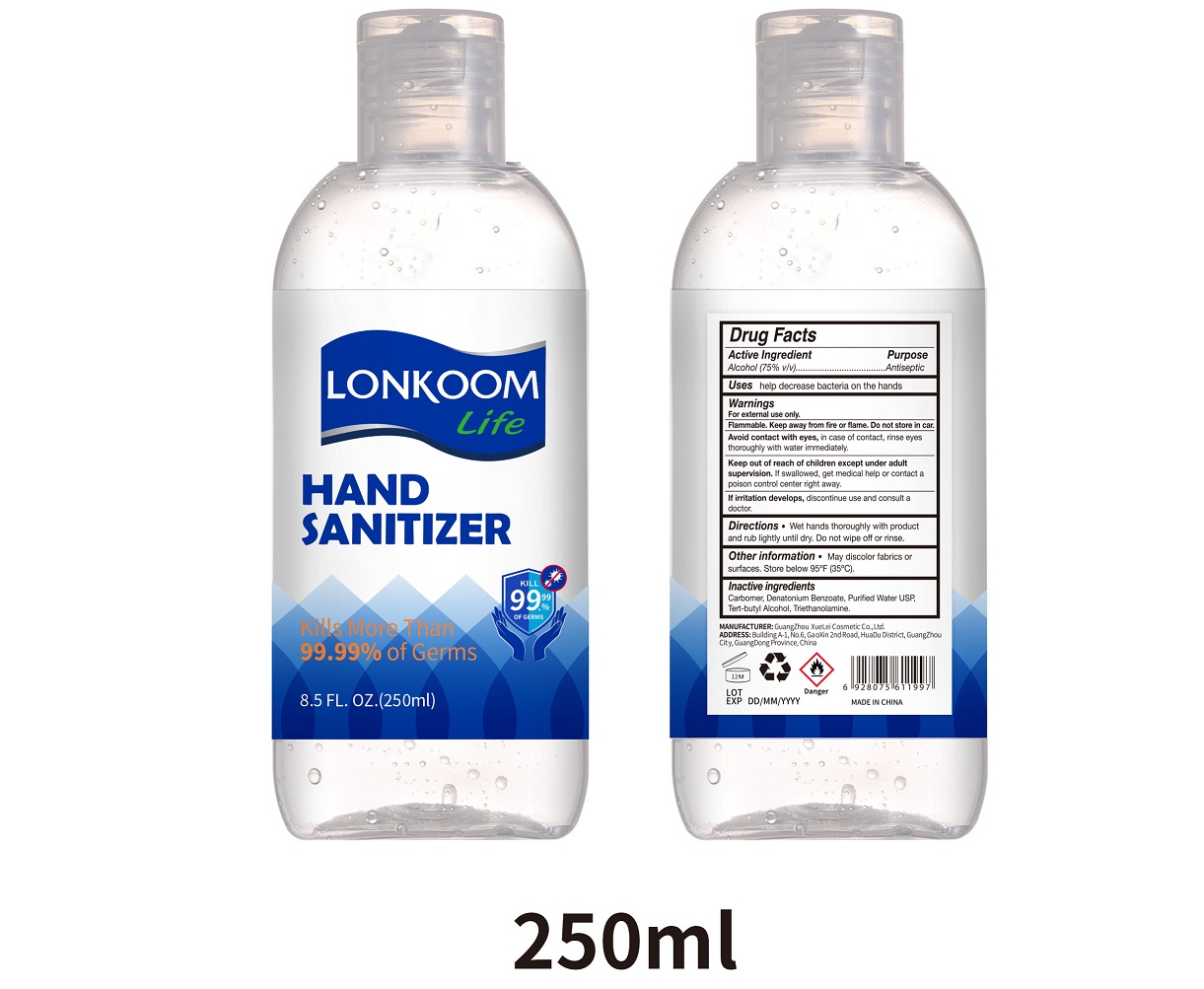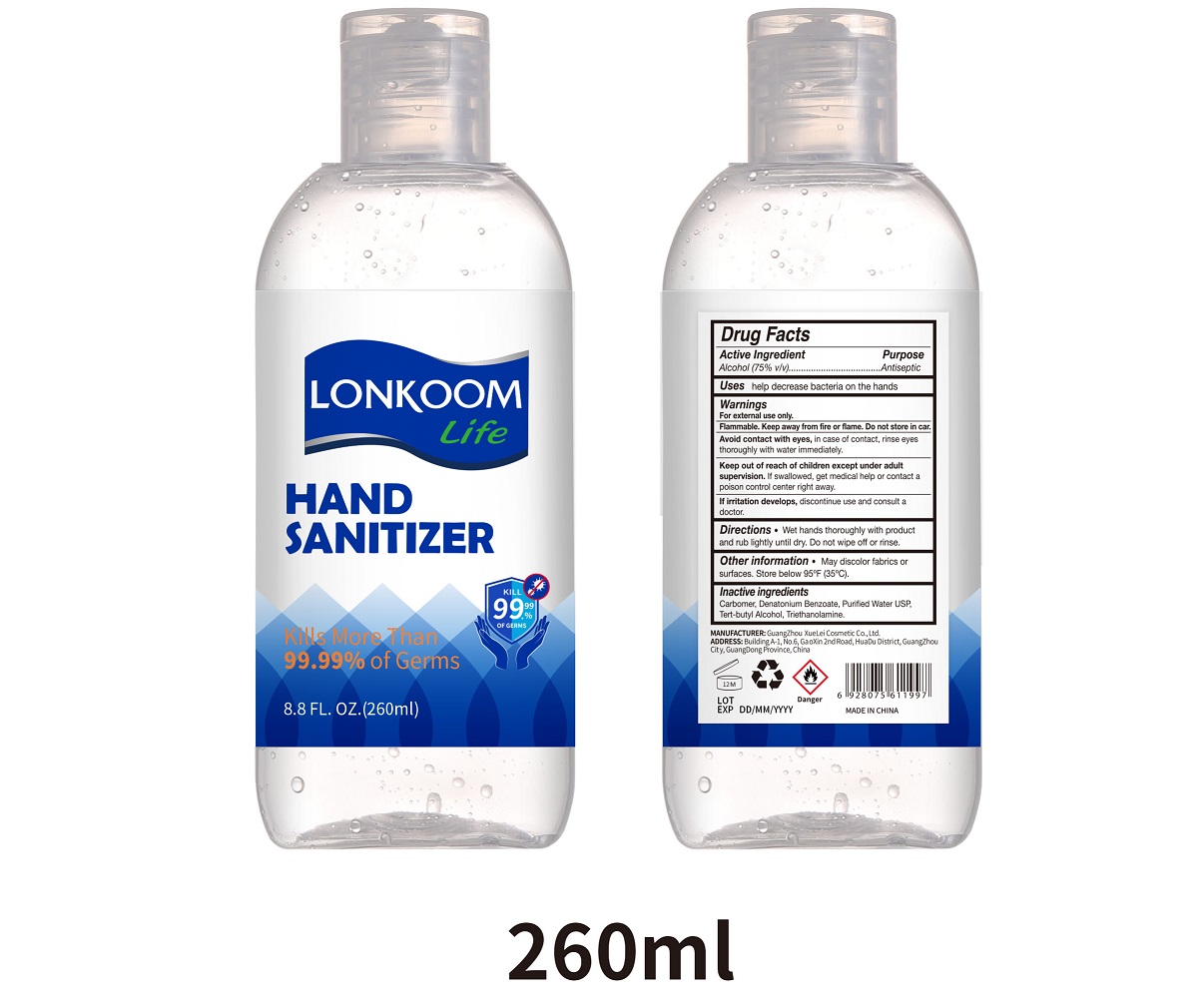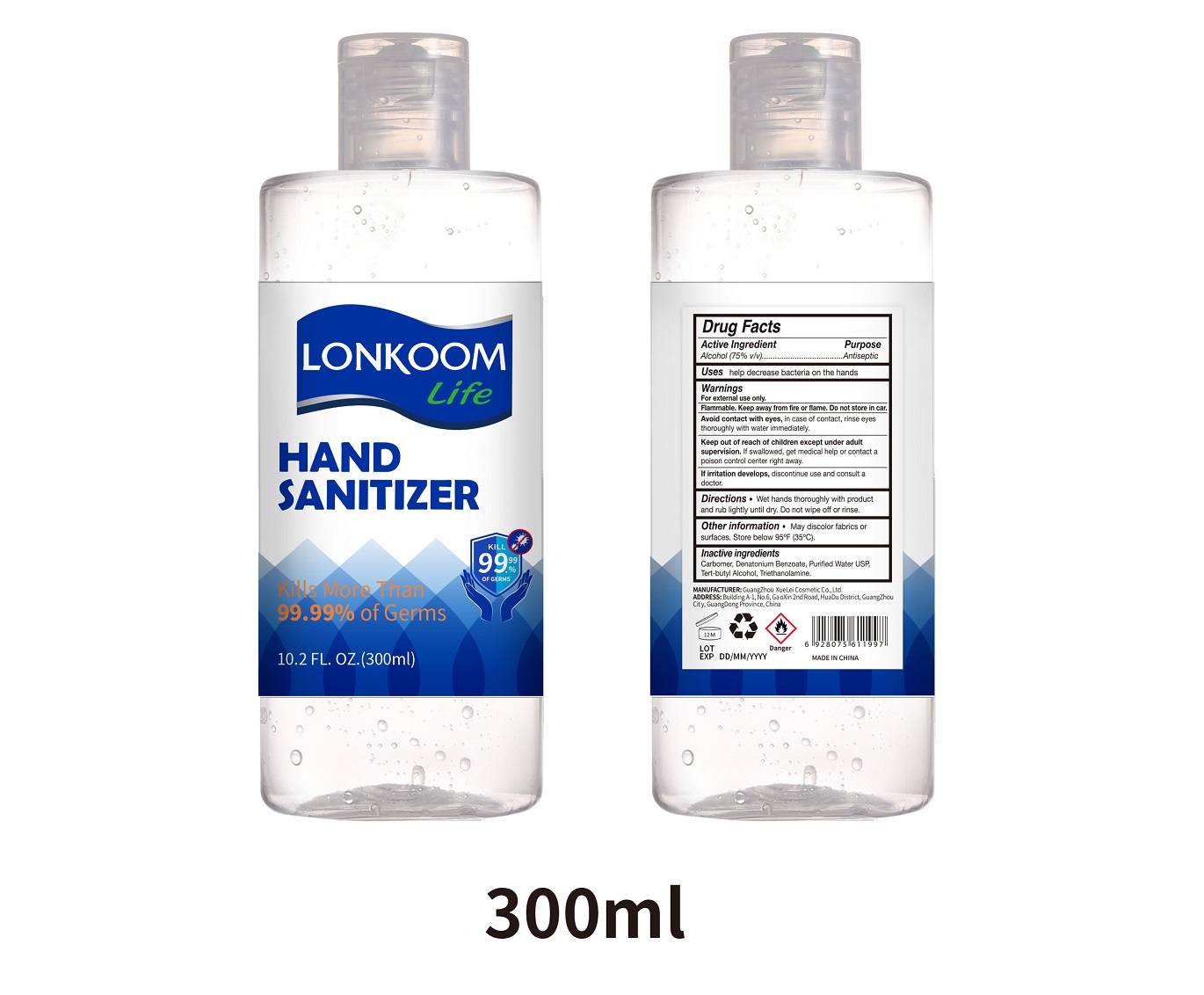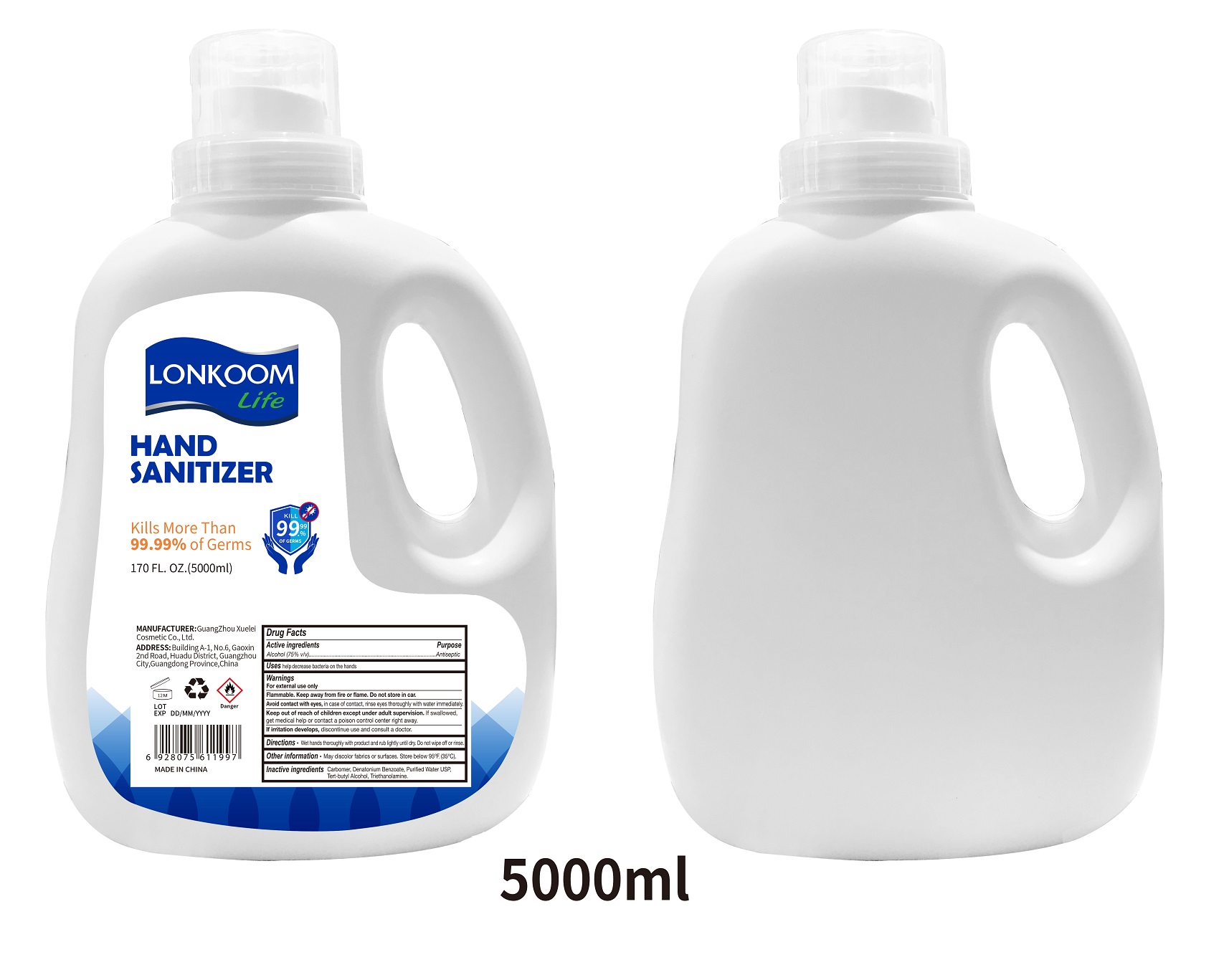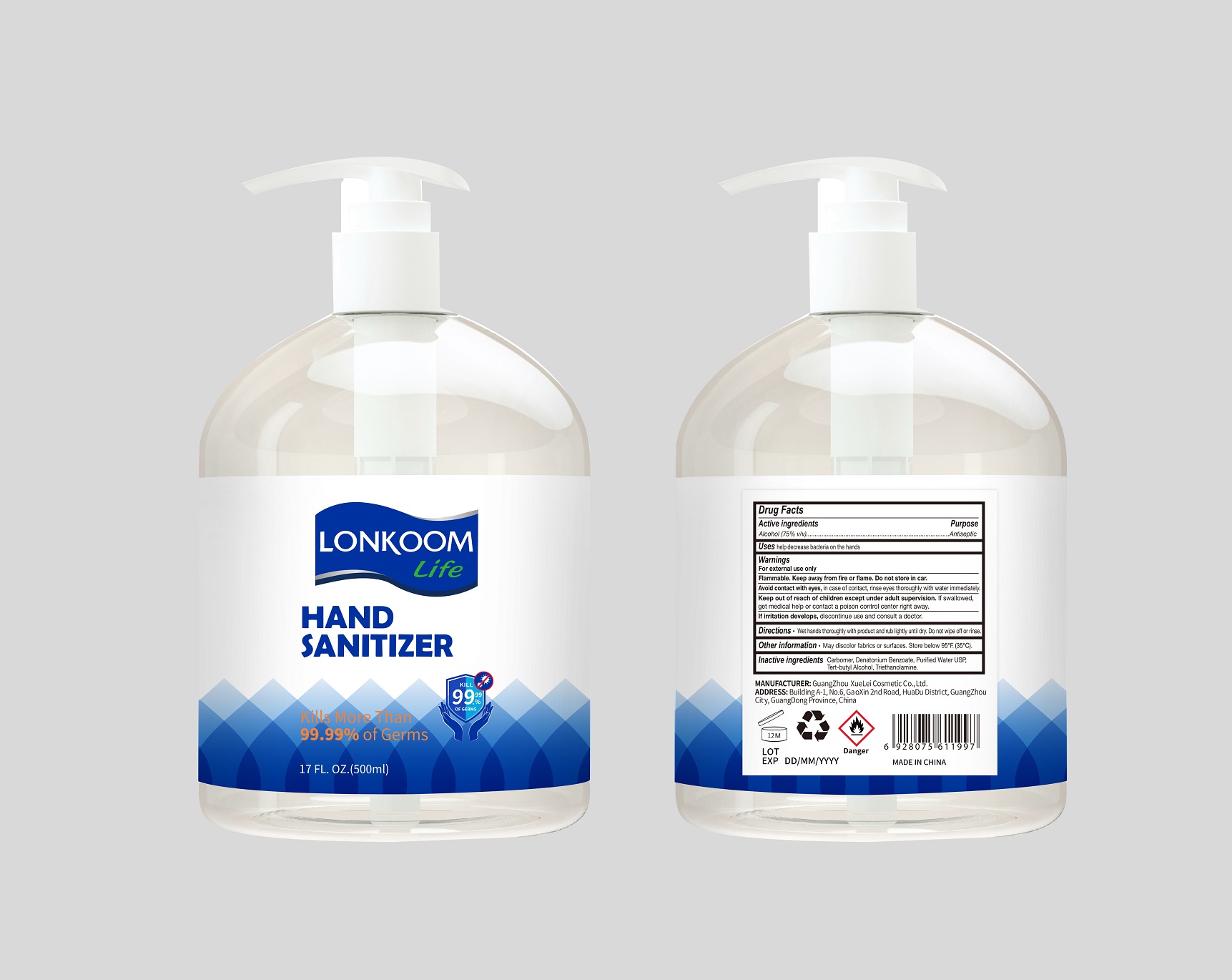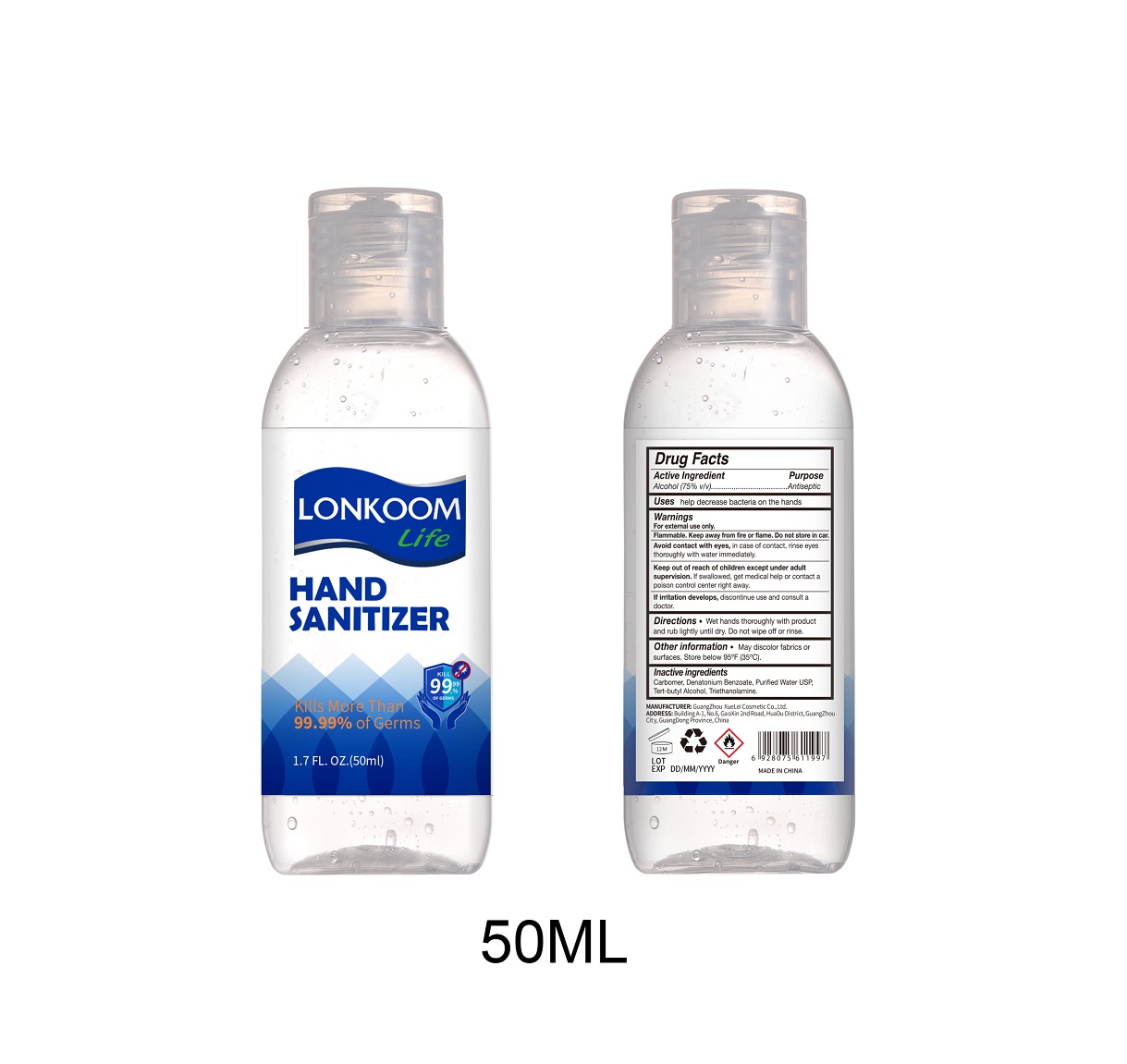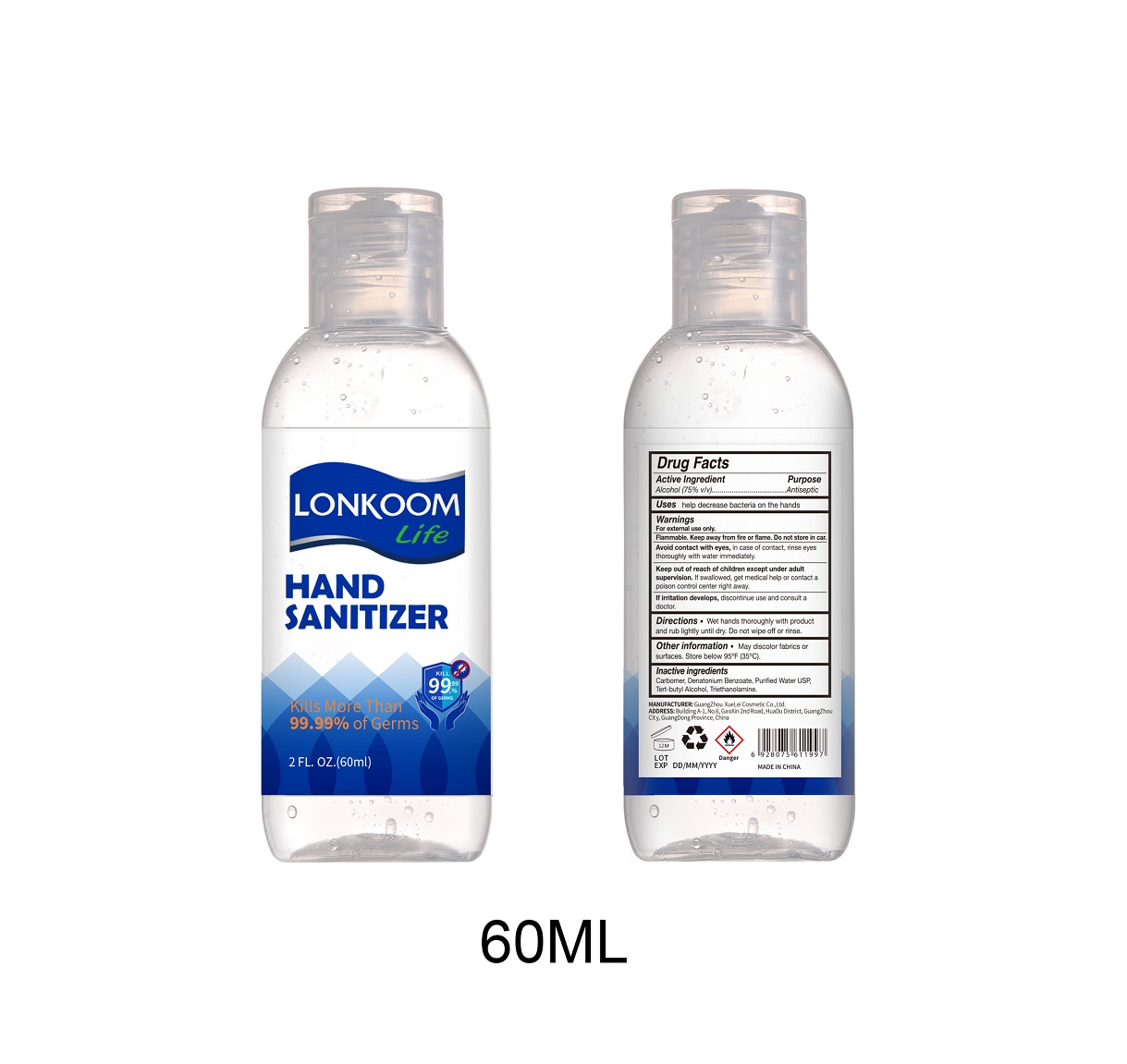 DRUG LABEL: HAND SANITIZER
NDC: 74658-010 | Form: GEL
Manufacturer: GUANGZHOU XUELEI COSMETIC CO.,LTD.
Category: otc | Type: HUMAN OTC DRUG LABEL
Date: 20211109

ACTIVE INGREDIENTS: ALCOHOL 75 mL/100 mL
INACTIVE INGREDIENTS: WATER 22.1937 g/100 mL; TERT-BUTYL ALCOHOL 0.0809 g/100 mL; CARBOMER HOMOPOLYMER TYPE B (ALLYL PENTAERYTHRITOL CROSSLINKED) 0.4 g/100 mL; TROLAMINE 0.22 g/100 mL; DENATONIUM BENZOATE ANHYDROUS 0.0004 g/100 mL

HAND SANITIZER

Active Ingredient

Alcohol（75% v//v）

Purpose

Antiseptic

Uses

help decrease bacteria on the hands

Warnings

For external use only.

Flammable. Keep away from fire or flame. Do not store in car.

Avoid contact with eyes, in case of contact, rinse eyes thoroughly with water immediately

Keep out of reach of children except under adult supervision. If swallowed, get medical help or contact a poison control center right away.

If irritation develops, discontinue use and consult a doctor.

Keep out of reach of children except under adult supervision. If swallowed, get medical help or contact a poison control center right away.

Directions

Wet hands thoroughly with product and rub lightly until dry. Do not wipe off or rinse.

Other Information

May discolor fabrics or surfaces. Store below 95 °F (35 ° C).

Inactive ingredients

Carbomer, Denatonium Benzoate, Purified Water USP, Tert-butyl Alcohol, Triethanolamine.

PACKAGE LABEL

50ml NDC: 74658-010-01

60ml NDC: 74658-010-02

236ml NDC: 74658-010-03

250ml NDC: 74658-010-04

260ml NDC: 74658-010-05

300ml NDC: 74658-010-06

500ml NDC: 74658-010-07

1000ml NDC: 74658-010-08

5000ml NDC: 74658-010-09